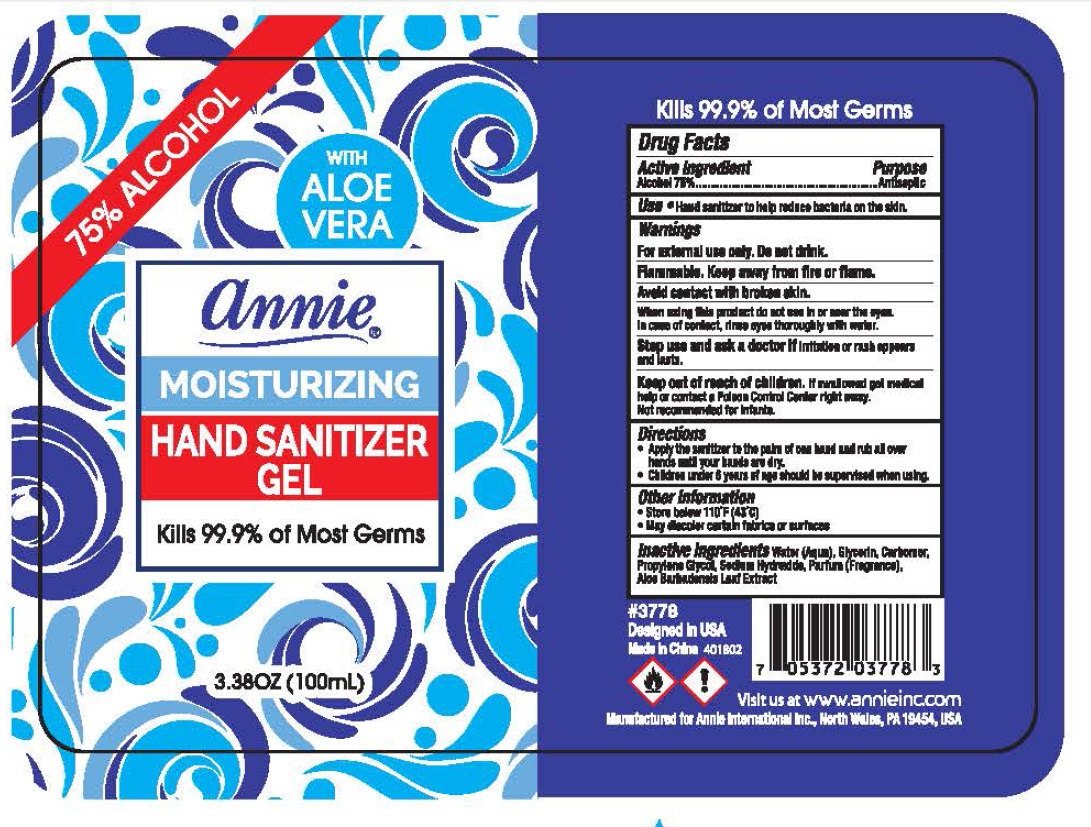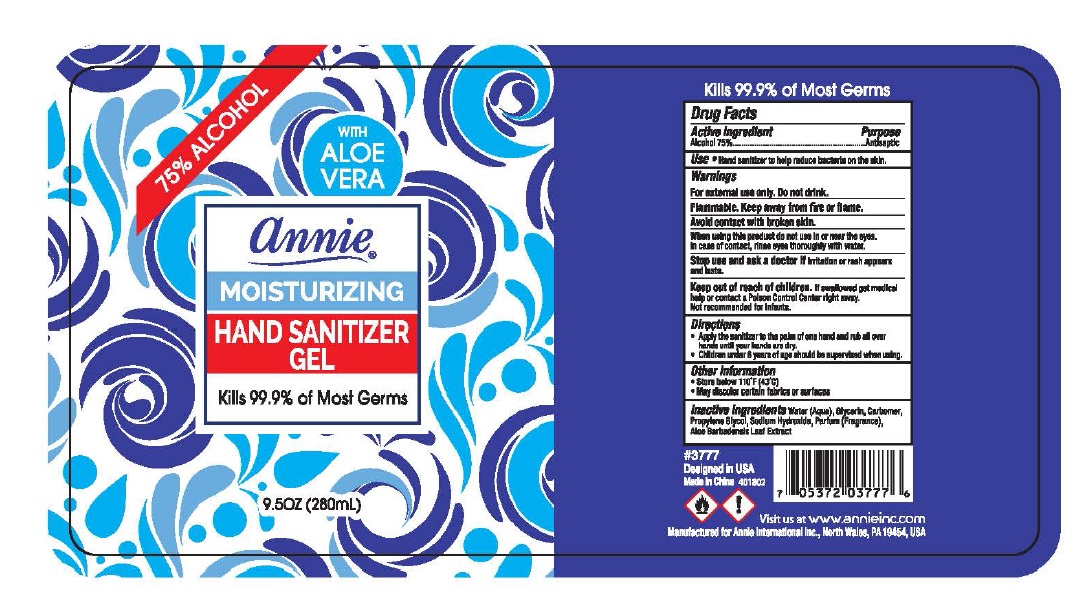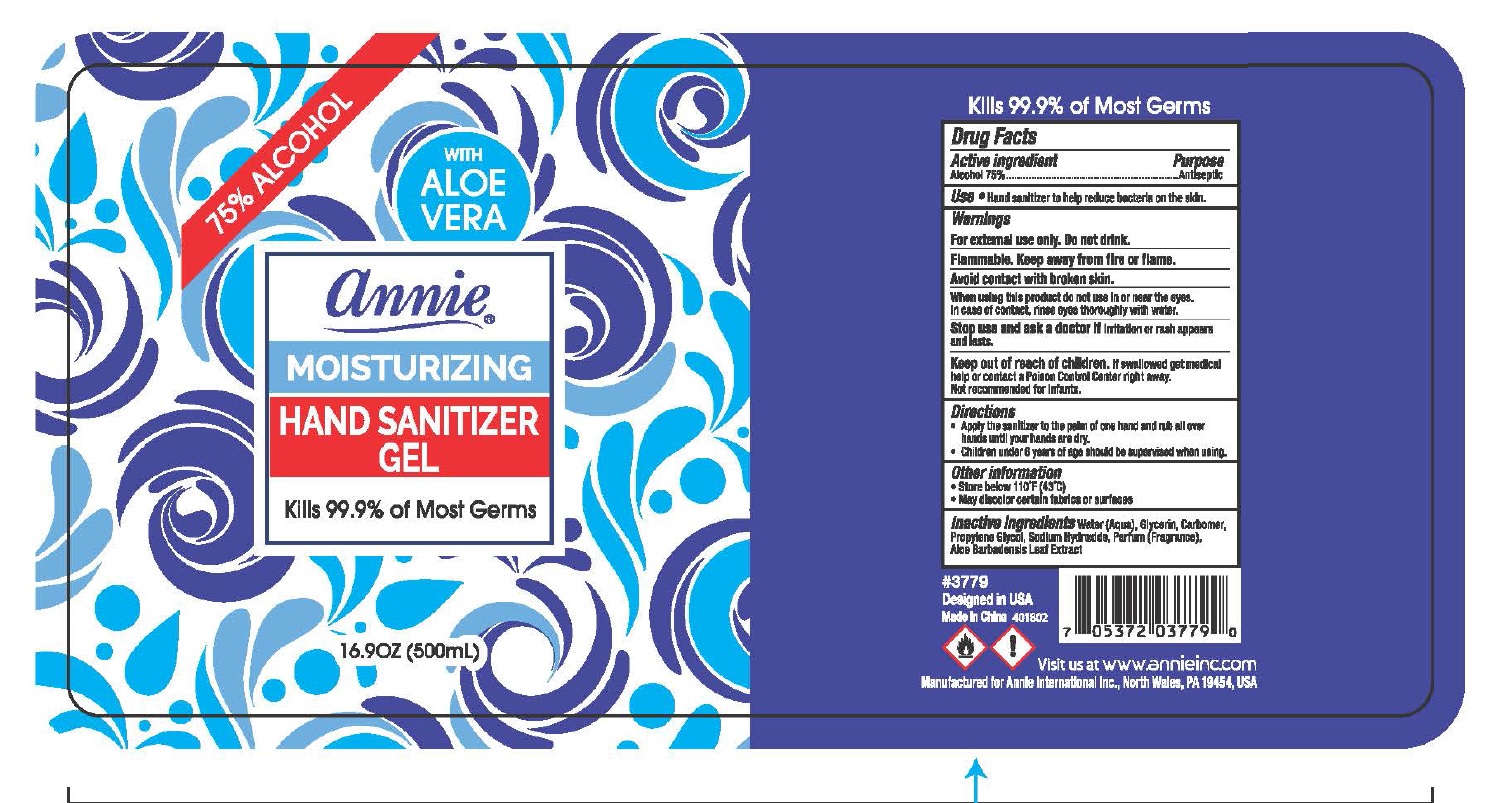 DRUG LABEL: Annie
NDC: 75629-075 | Form: GEL
Manufacturer: ANNIE INTERNATIONAL, INC
Category: otc | Type: HUMAN OTC DRUG LABEL
Date: 20200514

ACTIVE INGREDIENTS: ALCOHOL 70 mL/100 mL
INACTIVE INGREDIENTS: WATER; GLYCERIN; CARBOMER HOMOPOLYMER, UNSPECIFIED TYPE; PROPYLENE GLYCOL; SODIUM HYDROXIDE; ALOE VERA LEAF

Active Ingredient

Alcohol 75%

Purpose

Antiseptic

Use

Hand Sanitizer to help reduce bacteria on the skin

Warnings

Flammable. Keep away from fire or flame

For external use only.

When using this product

do not use it near the eyes. In case of contact with eyes, rinse eyes thoroughly with water.

Stop use and ask a doctor if

irritation or rash appears and lasts

Keep out of reach of children.

If swallowed, get medical help or contact a Poison Control Center right away.

Directions

- Apply the sanitizer to the palm of one hand and rub all over hands until your hands are dry
- Children under 6 years of age should be supervised when using

Other information

- Store below 110°F (43°C)
- May discolor certain fabrics or surfaces

Inactive ingredients

Water (Aqua), Glycerin, Carbomer, Propylene Glycol, Sodium Hydroxide, Parfum (Fragrance), Aloe Barbadensis Leaf Extract

Principal Display Panel

NDC 75629-075-03

annie®

MOISTURIZING HAND SANITIZER GEL WITH ALOE VERA

Kills 99.9% of Most Germs

3.38 OZ (100mL)

NDC 75629-075-09

annie®

MOISTURIZING HAND SANITIZER GEL WITH ALOE VERA

Kills 99.9% of Most Germs

9.5 OZ (280mL)

NDC 75629-075-17

annie®

MOISTURIZING HAND SANITIZER GEL WITH ALOE VERA

Kills 99.9% of Most Germs

16.91 OZ (500mL)